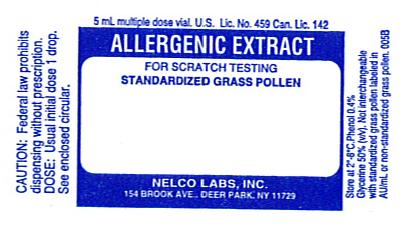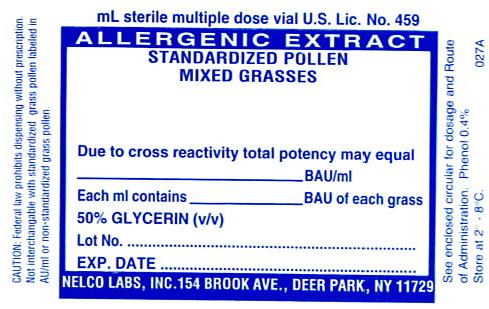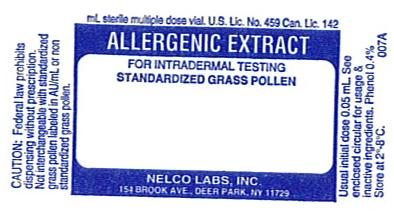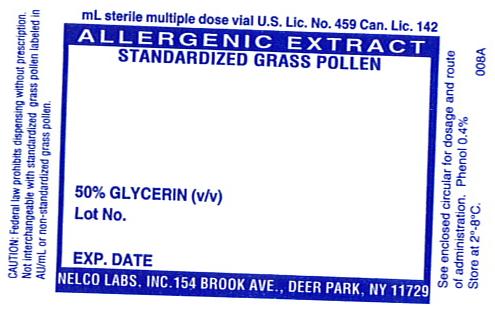 DRUG LABEL: Standardized Orchard Grass Pollen
NDC: 36987-2346 | Form: INJECTION, SOLUTION
Manufacturer: Nelco Laboratories, Inc.
Category: prescription | Type: HUMAN PRESCRIPTION DRUG LABEL
Date: 20091125

ACTIVE INGREDIENTS: DACTYLIS GLOMERATA POLLEN 10000 [BAU]/1 mL
INACTIVE INGREDIENTS: GLYCERIN; WATER; PHENOL; SODIUM CHLORIDE; SODIUM BICARBONATE; SODIUM PHOSPHATE, DIBASIC; POTASSIUM PHOSPHATE, MONOBASIC

Allergenic Extract

WARNINGS

Standardized allergenic extract is intended for use by physicians who are experienced in the administration of standardized (BAU/mL) allergenic extracts for immunotherapy and the emergency care of anaphylaxis, or for use under the guidance of an allergy specialist. For previously untreated patients, the initial dose must be based on skin testing as described in the dosage and administration section of this insert. Standardized Grass Pollen extract is NOT directly interchangeable with Grass Pollen extracts labeled in AU/mL, or with non-standardized Grass Pollen extracts.

This product should not be injected intravenously. Deep subcutaneous routes have proven to be safe. Sensitive patients may experience severe anaphylactic reactions resulting in respiratory obstruction, shock, coma and/or death. (See Adverse Reactions)

Serious adverse reactions should be reported to Nelco Laboratories immediately and a report filed to: MedWatch, The FDA Medical Product Problem Reporting Program, at 5600 Fishers Lane, Rockville, Md. 20852-9787, call 1-800-FDA-1088.

Extreme caution should be taken when using allergenic extracts for patients who are taking beta-blocker medications. In the event of a serious adverse reaction associated with the use of allergenic extracts, patients receiving beta-blockers may not be responsive to epinephrine or inhaled bronchodialators.(1) (See Precautions)

Allergenic extracts should be used with caution in patients with unstable or steroid-dependent asthma or with underlying cardiovascular disease. (See Contraindications)

DESCRIPTION

Standardized Grass Pollen Extracts include: Orchard (Dactylis glomerata), Perennial Rye (Lolium perenne), Timothy (Phleum pratense), Redtop (Agrostis alba), Kentucky (June) Bluegrass (Poa pratensis), Bermuda (Cynodon dactylon), Meadow Fescue (Festuca elatior), Sweet Vernal (Anthoxanthum odoratum). The standardized grass pollen extract is prepared by extracting raw pollen material at a ratio of either 1:5 w/v, 1:6.66 w/v or 1:10 w/v in Cocas fluid containing 0.5% NaCl, 0.275% NaHCO3, WFI and 0.4% phenol as preservative. Following extraction, a calculated amount of glycerin is added to make a 50%(v/v) glycerinated solution. Standardized Grass Pollen extracts have potency designations of 10,000 BAU/mL and 100,000 BAU/mL except Bermuda Grass (10,000 BAU/mL only). Extracts with a potency of 10,000 BAU/mL are diluted from the 100,000 BAU/mL lots with Glycerol Saline 50%(v/v). The Glycerol Saline 50%(v/v) solution consists of Glycerin and Salts and Buffered Diluent whose ingredients are 0.5% NaCl, 0.08% Na2HPO4, 0.036% KH2PO4, WFI and 0.4% phenol as a preservative. All extracts are aseptically filled in sterile containers. Standardized pollen extracts are intended for administration by prick-puncture or intradermal routes when used for diagnostic purposes and administered subcutaneously when used for immunotherapy injection.

Standardized grass pollen extracts labeled in BAU/mL are not interchangeable with grass pollen extracts labeled in AU/mL or with non-standardized grass pollen extracts. The Bioequivalent Allergy Unit (BAU), the potency unit used for all Standardized Pollen Extracts, replaces the previous unitage for these products. Bioequivalent Allergy Units were assigned to the FDA, Center for Biologics Evaluation and Research (CBER) reference extracts, based on quantitative intradermal skin test results. BAU's are intended to assure that the labeled unitage of different allergenic extracts will correspond to the expected clinical response in sensitive patients. References labeled 10,000 BAU/mL can be diluted one half million fold to produce an intradermal sum of erythema diameter response of 50mm in highly puncture reactive subjects. 100,000 BAU/mL can be diluted 1:5 million fold to yield the same intradermal response.(2) The assignment of BAU/mL to standardized grass pollen extracts, is accomplished by an ELISA assay comparing the extract to the CBER reference.

Previously, the potency / concentration of grass mixtures was designated based on the manufacturing strength, e.g. 1:10 w/v or 1:20 w/v, or in PNU's/mL. For grass mixtures containing standardized extracts, the potency will reflect the contribution of each individual component in the mixture, i.e., the actual potency of each component will be listed on a per mL basis. In addition, because the individual components may be cross-reactive, an additional caution statement, "due to cross reactivity, total potency may be 100,000 BAU/mL," will be added to the label.

CLINICAL PHARMACOLOGY

The mode of action of allergenic extracts is still under investigation. The pharmacological action of allergenic extracts used diagnostically is based on the liberation of histamine and other substances when the allergen reacts with IgE antibodies attached to the mast cells. When allergenic extracts are used for therapeutic immunotherapy, the effect is an increase in immunoglobulin G (IgG) and an increased T suppresser lymphocyte which interferes with the allergic response.(3) Although immunotherapy may be considered as immunosuppression, in which the production of allergen-specific antibody is inhibited, the mechanism of the clinical effectiveness of immunotherapy remains under investigation. Assignment of BAU/mL potency designation was determined based on Puncture and Intradermal Data with CBER Grass References.(2)

Puncture & Intradermal Data with CBER Grass References

A. Puncture Data with 10,000 BAU/mL Grass Extracts (bifurcated needle)

Reference Pollen | FDA Lot # | N | P Σ E (mm) Mean | P Σ E (mm) Range | P Σ W (mm) Mean | P Σ W (mm) Range
Bermuda | E4-Ber | 15 | 90.3 | 43-123 | 15.7 | 7-31
June | E3-Jkb | 15 | 77.3 | 47-107 | 15.9 | 6-28
Meadow Fescue | E4-Mf | 15 | 81.1 | 57-115 | 11.9 | 7-22
Orchard | E4-Or | 15 | 84.3 | 57-111 | 14.1 | 9-19
Perennial Rye | E10-Rye | 15 | 92.3 | 73-135 | 17.5 | 6-36
Redtop | E4-Rt | 15 | 77.1 | 42-98 | 14.1 | 8-19
Sweet Vernal | E4-Sv | 15 | 81.2 | 28-123 | 15.7 | 8-30
Timothy | E6-Ti | 15 | 88.3 | 51-109 | 16.9 | 8-40

B. Intradermal Dose (BAU50) of CBER Grass References for 50 mm Sum of Erythema

Reference Pollen | FDA Lot # | BAU50/mL Mean | BAU50/mL Range
Bermuda | E4-Ber | 0.02 | 0.4-0.0003
June | E3-Jkb | 0.02 | 0.1-0.004
Meadow Fescue | E4-Mf | 0.02 | 0.9-0.002
Orchard | E4-Or | 0.02 | 1.9-0.002
Perennial Rye | E10-Rye | 0.02 | 0.7-0.002
Redtop | E4-Rt | 0.02 | 0.8-0.004
Sweet Vernal | E4-Sv | 0.02 | 1.0-0.002
Timothy | E6-Ti | 0.02 | 0.6-0.002

C. Potency of Selected Glycerinated Non-Standardized Grasses distributed by Nelco Laboratories, Inc.

Extract | Weight/ Volume | # of Lots | Range (BAU/mL)
Orchard | 1:10 | 3 | 144,200-155,300
Bermuda | 1:20; 1:10 | 3 | 7,800-12,560
Sweet Vernal | 1:10 | 3 | 180,600-236-200
Timothy | 1:10 | 2 | 99,100-110,200
Perennial Rye | 1:20; 1:10 | 2 | 77,900-162,100
June | 1:20; 1:10 | 3 | 79,000-111,500
Redtop | 1:20; 1:10 | 3 | 179,900-300,500
Meadow Fescue | 1:20 | 2 | 128,800-294,800
* Note: These extracts were previously distributed.

The potency of the glycerinated non-standardized grass extracts are equivalent to or exceed the potency for standardized grass pollen extract (Range for equivalence to CBER reference labeled 100,000 BAU/mL is 67,300 to 148,600, and range for equivalence to CBER reference labeled 10,000 BAU/mL is 6,730 to 14,860).

INDICATIONS AND USAGE

Standardized Pollen Extract is intended for use in the diagnosis and therapy of pollen allergic patients as established by allergy history and skin test reactivity. Standardized Grass Pollen extracts labeled in BAU/mL are not interchangeable with Grass Pollen extracts labeled in AU/mL or with non-standardized Grass Pollen extracts. The 10,000 BAU/mL dose form is indicated for percutaneous testing. If negative, 100,000 BAU/mL dose form can be used for percutaneous testing. For immunotherapy, availability of 10,000 and 100,000 BAU/mL dosages facilitates safe switching. (See Dosage & Administration)

The use of standardized grass pollen extracts is indicated for hyposensitization treatment and may be used as part of the over-all management of the allergic patient. Treatment of grass sensitive patients consists of using specific standardized grass products of up to and including doses of 100,000 BAU/mL (up to 10,000 BAU/mL for Bermuda grass) or stock mixtures of standardized grass products. Stock mixtures of standardized grass extracts are particularly useful in hyposensitization treatment when multiple allergies to grasses are diagnosed. For previously untreated patients, the 10,000 BAU/mL concentrates can be used to formulate dosages. If tolerated, the concentrates can be inceased to 100,000 BAU/mL dose formulation.

CONTRAINDICATIONS

Standardized Pollen extract should not be used if the patient has asthma, cardiovascular disease, emphysema, diabetes, bleeding diathesis or pregnancy, unless a specific diagnosis of type 1 allergy to Pollen is made based on skin testing and the benefits of treatment outweigh the risks of an adverse reaction during testing or treatment. Pollen extract is not indicated for use in patients who are not clinically allergic to pollen or who are not skin reactive to pollen. Limitations on treatment should be considered when treating the very young, or geriatric patients or those suffering from auto-immune disorders or severe and unstable allergic disorders.

WARNINGS

Concentrated extracts must be diluted with sterile diluent prior to first use on a patient for treatment or intradermal testing.

DO NOT INJECT INTRAVENOUSLY.

All concentrates of allergenic extracts have the ability to cause serious local and systemic reactions including death in sensitive patients.(3) (See Adverse Reactions)

Standardized Pollen extracts should be used with caution when treating patients who exhibit hypersensitivity to standardized pollen extracts as confirmed by diagnostic testing.

An allergenic extract should be temporarily withheld from patients or the dose of the extract adjusted downward if any of the following conditions exist: (1) Severe symptoms of rhinitis and/or asthma (2) Infections or flu accompanied by fever and (3) Exposure to excessive amounts of clinically relevant allergen prior to a scheduled injection.

PRECAUTIONS

General: Epinephrine 1:1000 should be available as well as personnel trained in administering emergency treatment. Allergenic Extracts are not intended for intravenous injections. For safe and effective use of allergenic extracts, sterile diluents, sterile vials, sterile syringes should be used and aseptic precautions observed when making a dilution and/or administering the allergenic extract injection. A sterile tuberculin syringe graduated in 0.1 mL units to measure each dose for the prescribed dilution should be used.

To reduce the risk of an occurrence of adverse reactions, begin with a careful personal history plus a physical exam. Confirm your findings with scratch or intradermal skin testing. Patients should be observed for 30 minutes after any test.

Information for Patients: All concentrates of allergenic extracts including standardized pollen extracts, have the potential to cause serious local and systemic reactions including death, in sensitive patients. To minimize this potential hazard, the relative sensitivity of the patient must be assessed from an allergic history and clinical observations. In certain individuals, life-threatening reactions may occur. Patients should be informed of this risk prior to skin testing and immunotherapy. Patients should be instructed to recognize adverse reaction symptoms that may occur and to report all adverse reactions to a physician and to wait in the office at least 30 minutes after an injection.

Drug Interactions: Antihistamines and Hydroxyzine can significantly inhibit the immediate skin test reactions as they tend to neutralize or antagonize the action of histamine.(3) This effect has been primarily documented when testing was performed within 1 to 2 hours after drug ingestion, although partial inhibition of the skin test reaction had been observed for longer periods. Epinephrine injection inhibits the immediate skin test reactions for several hours. Patients on delayed absorption antihistamine tablets should be free of such medication for 48 hours before testing. Patients using Astemizole (Hismanal) may experience prolonged suppression and should be free from such medication for up to 6 to 8 weeks prior to testing. Refer to package insert from a long acting antihistamine manufacturer for more information.

Extreme caution should be taken when using allergenic extracts in patients who are taking beta-blockers. Patients receiving beta-blockers may not be responsive to epinephrine or inhaled bronchodialators.

Carcinogenesis, mutagenesis, impairment of fertility.

Long term studies in animals have not been conducted with allergenic extracts, including Pollen extracts, to determine their potential carcinogenicity, mutagenicity or impairment of fertility.

Pregnancy: Category C. Animal reproduction studies have not been conducted with allergenic extract. It is not known whether this extract can cause fetal harm when administered to a pregnant women or can effect reproduction capacity. Due to histamines ability to induce uterine contractions, allergenic extract should be given to pregnant women only if clearly needed.

Nursing Mothers: It is not known whether this drug appears in human milk. Because many drugs are detected in human milk, caution should be exercised when Allergenic Extracts are administered to a nursing woman. There are no current studies on extract components in human milk, or their effect on the nursing infant.

Pediatric Use: Allergenic extracts have been used in children over two years of age.(4)

ADVERSE REACTIONS

Adverse systemic reactions usually occur within minutes and consist primarily of allergic symptoms such as: generalized skin erythema, urticaria, pruritus, angioedema, rhinitis, wheezing, laryngeal edema, itching of nose and throat, breathlessness, dyspnea, coughing, hypotension and marked perspiration. Less commonly, nausea, emesis, abdominal cramps, diarrhea and uterine contractions may occur. Severe reactions may cause anaphylaxis or shock and loss of consciousness. In rare instances this may result in death.

The treatment of systemic allergic reactions is dependent upon the system complex. Antihistamines may offer relief of recurrent urticaria, associated skin reactions and gastrointestinal symptoms. Corticosteroids may provide benefit if symptoms are prolonged or recurrent. (See Overdosage)

Local Reactions consisting of erythema, itching, swelling tenderness and sometimes pain may occur at the injection site. These reactions may appear within a few minutes to hours and persist for several days. Local cold applications and oral antihistamines may be effective treatment. For marked and prolonged local reactions the use of antihistamines or anti-inflammatory medications may be indicated.

Serious adverse reactions should be reported to Nelco Laboratories immediately and a report can be filed to: MedWatch, The FDA Medical Product Problem Reporting Program, at 5600 Fishers Lane, Rockville, MD 20852-9787, call 1-800-FDA-1088.

OVERDOSAGE

An overdose can cause both local and systemic reactions. An overdose is prevented by careful observation and questioning the patient about reactions to previous extract injections.

If systemic or anaphylactic reaction does occur, apply a tourniquet above the site of injection and inject intramuscularly or subcutaneously 0.3 to 0.5mL of 1:1000 epinephrine hydrochloride into the opposite arm. The dose may be repeated in 5-10 minutes if necessary. Loosen the tourniquet at least every 10 minutes. The epinephrine hydrochloride 1:1000 dose for infants to 2 years is 0.05 to 0.1mL, for children 2 to 6 years it is 0.15mL, for children 6-12 years it is 0.2mL. Patients unresponsive to epinephrine may be treated with intravenous bronchodilators. Studies on asthmatic subjects reveal that plasma concentrations of theophylline of 5 to 20 µg/mL are associated with therapeutic effects. Toxicity is particularly apparent at concentrations greater than 20 µg/mL. A loading dose of aminophylline of 5.8 mg/kg intravenously followed by 0.9 mg/kg per hour results in plasma concentrations of approximately 10 µg/mL for patients not previously receiving theophylline. (Mitenko, Ogilive 1973; Nicholoson, Chick 1973)

Other beta-adrenergic drugs such as Isoproterenol, Isoetharine, or Albuterol may be used by inhalation. The usual dose to relieve broncho-constriction in asthma is 0.5mL of the 0.5% solution for Isoproterenol HCl. The Albuterol inhaler delivers approximately 90mcg of Albuterol from the mouthpiece. The usual dosage for adults and children would be two inhalations repeated every 4-6 hours. Isoetharine supplied in the Bronkometer unit delivers approximately 340mcg Isoetharine. The average dose is one to two inhalations. Persistent wheezing may necessitate intravenous aminophylline treatment. For profound shock and hypotension, intravenous fluids, vasopressors and oxygen may also be needed. Respiratory obstruction not responding to parenteral or inhaled bronchodilators may require oxygen, intubation and the use of life support systems.

DOSAGE AND ADMINISTRATION

It is imperative that the physician determine a safe initial dose. Patients being switched from one lot of Standardized Pollen to another lot of Standardized Pollen (from the same or different manufacturers) should have the initial dose from the new lot reduced by 75%. For patients being switched from non-standardized extract to a standardized extract, the selection of dose needs to be based on the dose of the extract currently administered and the relative potency with regards to the standardized extract. (See Clinical Pharmacology Table C for a comparison of standardized and non-standardized pollen extracts). Side by side comparison of wheal and erythema by skin testing of standardized and non-standardized extract can be carried out to determine comparability of doses selected.

For safe and effective use of allergenic extracts, sterile solutions, vials, syringes, etc. should be used and aseptic precautions followed when making dilution's and giving injections. The usual precautions to be observed in administering extracts are necessary. A sterile tuberculin syringe graduated in 0.1mL units to measure each dose for the prescribed dilution should be used.

After therapeutic injections patients should always be observed for at least 30 minutes. If adverse reactions appear, the next therapeutic injection of extract should be reduced to the dose which does not elicit a reaction and subsequent doses increased more slowly.

Recommended dosage and range: (Scratch or Prick tests)

The general method of making a scratch test is to first scarify the skin and then apply a drop of extract to the scratch. Make scarifications at least 2.5 cm apart. Hold the scarifier between thumb and index finger, press the sharp edge of the instrument against the skin and twirl instrument rapidly. The scratch should disrupt the outer layers of epidermis but should not produce immediate oozing of blood. One drop (0.05mL) of extract is rubbed or applied into each scratch. Always apply a control scratch with each test set. Sterile Diluent (for a negative control) is used in exactly the same way as an active test extract. Histamine may be used as a positive control. Scratch or prick test sites should be examined at 15 and 30 minutes. To prevent excessive absorption, wipe off antigens producing large reactions as soon as the wheal appears. Record the size of the reaction.

The concentration of Standardized Pollen extract for Scratch or Prick-puncture testing is prepared using 10,000 BAU/mL. If negative, 100,000 BAU/mL can be used to determine sensitivity of the patient.

Recommended dosage and range: (Intradermal tests)

Patients with a negative scratch or prick-puncture test:

Patients who do not react to a valid scratch or prick- puncture test should be tested intradermally with 0.05mL of a 50 BAU/mL extract solution. If this test is negative, a second intradermal test may be performed using a 100 BAU/mL extract dilution. The negative puncture test control must be diluted appropriately for intradermal use.

To prepare a 50 BAU/mL dilution from Nelco's

10,000 BAU/mL vial:

Take 5.0 mL of the 10,000 BAU/mL + 5.0mL of diluent

equals Vial A at 5,000 BAU/mL.

Take 1.0 mL of Vial A + 9.0 mL diluent equals

Vial B at 500 BAU/mL.

Take 1.0 mL of Vial B + 9.0 mL diluent equals

Vial C at 50 BAU/mL.

Patients tested only by the intradermal method: (See table B) Patients being suspected of being highly allergic should be tested with 0.05 mL of a 0.1 BAU/mL dilution. A negative test should be followed by repeat tests using progressively stronger concentrations until the maximal recommended strength of 100 BAU/mL is reached. The negative puncture test control must be diluted appropriately for intradermal use. To prepare this dilution follow the tenfold dilution series chart for therapeutic allergens.

Skin tests are graded in terms of the wheal and erythema response noted at 10 to 20 minutes. Wheal and erythema size may be recorded by actual measurement as compared with positive and negative controls.

Preparation Instructions: To prepare a dilution for intradermal and therapeutic use, one starts with 10,000 BAU/mL stock concentrate and makes a 1:10 dilution by adding 1.0 mL of the concentrate to 9.0mL of sterile diluent. Subsequent dilutions are made in similar manner.

TEN-FOLD DILUTION SERIES
Dilution | Extract | Diluent mL | BAU/mL
0 | Concentrate | 0 | 10,000
1 | 1 mL concentrate | 9 | 1,000
2 | 1 mL dilution #1 | 9 | 100
3 | 1 mL dilution #2 | 9 | 10
4 | 1 mL dilution #3 | 9 | 1
5 | 1 mL dilution #4 | 9 | 0.1
6 | 1 mL dilution #5 | 9 | 0.01

Recommended dosage and range: (Therapeutic)

Dosage of allergenic extracts is a highly individualized matter and varies according to the degree of sensitivity of the patient, the clinical response and tolerance to the extract administered during the injection regimen. The dosage of allergenic extract does not vary significantly with the respiratory allergic disease under treatment. In patients who appear to be highly sensitive by history and skin test, the initial dose of the extract should be 0.05mL of 5 BAU/mL which results in a dosage of 0.25 BAU. Patients with lesser sensitivity may be started using 1 BAU/mL. The amount of allergenic extract is increased at each injection by not more than 50%-100% of the previous amount, and the next increment is governed by the response to the last injection. Any evidence of systemic reaction is an indication for a significant reduction (at least 50%) in the subsequent dose. Any evidence of a local or generalized reaction requires a reduction in dosage. After therapeutic injections, patients should always be observed for at least 20 minutes. If adverse reactions appear, the next therapeutic injection of extract should be reduced to the dose which dose not elicit a reaction and subsequent doses increased more slowly. The upper limits of dosage have not been established. Doses larger than 0.2 mL of 10,000 BAU/mL may be painful due to glycerin content. Dosage use of up to 100,000 BAU/mL is determined by patient response and administered at the discretion of the physician.

Suggested Dosage Charts *(Note Disclaimer)

*This is a suggested dose chart only. Dose regimen has not been subjected to adequate and well controlled studies to determine safety and efficacy.

Please read entire instructions before commencing immunotherapy. Observe patients for 30 minutes after an injection. Note: Certain individuals may not tolerate this suggested schedule. The physician may need to adjust both the dosage and interval accordingly.

Suggested Treatment Schedule
Vial # | Injection # | Volume (mL)
1 (5 BAU/mL) | 1 | 0.05
1 | 2 | 0.10
1 | 3 | 0.15
1 | 4 | 0.20
1 | 5 | 0.30
1 | 6 | 0.40
1 | 7 | 0.50
2 (50 BAU/mL) | 8 | 0.05
2 | 9 | 0.10
2 | 10 | 0.15
2 | 11 | 0.20
2 | 12 | 0.30
2 | 13 | 0.40
2 | 14 | 0.50
3 (500 BAU/mL) | 15 | 0.05
3 | 16 | 0.10
3 | 17 | 0.15
3 | 18 | 0.20
3 | 19 | 0.30
3 | 20 | 0.40
3 | 21 | 0.50
4 (5,000 BAU/mL) | 22 | 0.05
4 | 23 | 0.07
4 | 24 | 0.10
4 | 25 | 0.15
4 | 26 | 0.20
4 | 27 | 0.25
4 | 28+++ | 0.25

Note: Maintenance dose is that dose which provides symptomatic relief or the strongest dose that can be tolerated by the patient. Therefore, a physician must determine each patient's maintenance dose.

Intervals between doses: The optimal interval between doses of allergenic extract has not been definitely established. However, as it is customary practiced, injections are given once or twice per week until the maintenance dose of extract is reached. At this time, the injection interval may be increased to 2 weeks, then 3 weeks and finally to 4 weeks. If the patient does not return for 6-8 weeks after the last injection, the dose should be reduced to 25% of the last dose. If longer than 8 weeks, a dose reduction of 1,2, or 3 dilutions may be made depending on a consideration of the components and the patient's sensitivity.(3) The dosage and the interval between injections may need to be modified according to the clinical response of the patient. When switching patients to a new extract the initial dose should be reduced 3/4 so that 25% of previous dose is administered.

Duration of Treatment: The usual duration of treatment has not been established. A period of two or three years of injection therapy constitutes an average minimum course of treatment.

Parenteral drug products should be inspected visually for particulate matter and discoloration prior to administration, whenever solution and container permit.

HOW SUPPLIED

Diagnostic Allergens:

Scratch or Prick test:

10,000 BAU/mL or 100,000 BAU/mL contained in

50% glycerin (v/v)

in 5mL dropper vials.

Intradermal test:

100 BAU/mL in 5mL or 10mL sterile multiple dose vials.

Concentrate of Extract for Therapeutic Use Allergens:

10,000 BAU/mL and 100,000 BAU/mL are supplied in 5mL, 10mL, 50mL multiple dose vials.

STORAGE

The expiration date of Standardized Pollen extract containing 10,000 BAU/mL or 100,000 BAU/mL in 50% glycerin (v/v) is listed on the container label. Store extracts upon arrival at 2° to 8 °C and keep them in this range during office use.

WARRANTYWe warrant that this product was prepared and tested according to the standards of the FDA and is true to label. Because of biological differences in individuals and because allergenic extracts are manufactured to be potent and because we have no control over the conditions of use, we cannot and do not warrant either a good effect or against an ill effect following use.

REFERENCES

1. Jacobs, Robert L., Geoffrey W.Rake,Jr., et.al. Potentiated Anaphylaxis in Patients with Drug-induced Beta-adrenergic Blockade. J.Allergy & Clin. Immunol., 68(2): 125-127. August 1981.

2. Turkeltaub,P., Rastogi,S. Quantitative Intradermal Procedure for Evaluation of Subject Sensitivity to Standardized Allergenic Extracts and for Assignment of Bioequivalent Allergy Units to Reference Preparations using ID50EAL. Methods & Procedures Manual, CBER,1993.

3. Lockey, R.F., Bukantz, S.C., Allergen Immunotherapy. New York,NY: Marcel Dekker Inc., 1991.

4. Murray,A.B., Ferguson,A., Morrison, B., The frequency and severity of cat allergy vs dog allergy in atopic children. J. Allergy Clin. Immunolo: 72, 145-9, 1983.

5. Reid,M.J., Lockey,R.F., Turkeltaub,P.C., Platts-Mills,T.A.E., Survey of fatalities from skin testing and immunotherapy 1985-1989. Journal of Allergy Clin. Immunol. 92 (1): 6-15, July 1993.